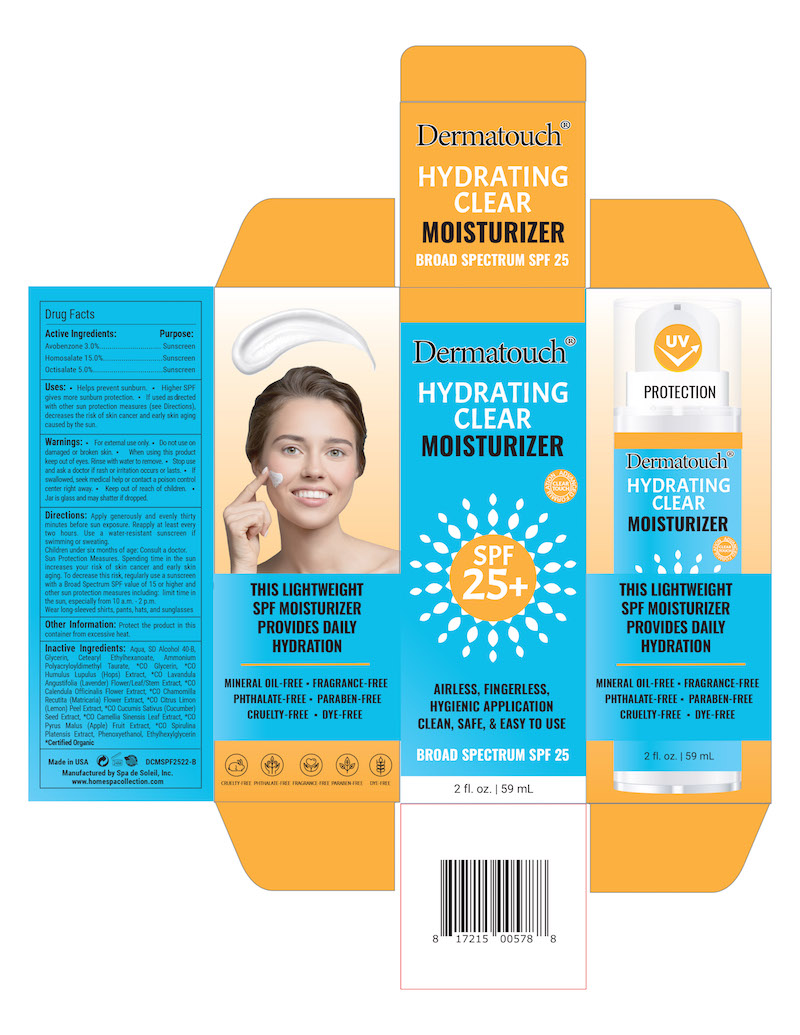 DRUG LABEL: Dermatouch Hydrating Clear Moisutrizer SPF 25
NDC: 68062-8309 | Form: LOTION
Manufacturer: Spa de Soleil
Category: otc | Type: HUMAN OTC DRUG LABEL
Date: 20260121

ACTIVE INGREDIENTS: OCTISALATE 2.5 mg/50 mL; AVOBENZONE 1.5 mg/50 mL; HOMOSALATE 7.5 mg/50 mL
INACTIVE INGREDIENTS: LAVANDULA ANGUSTIFOLIA FLOWER; CETEARYL ETHYLHEXANOATE; MATRICARIA CHAMOMILLA LEAF; GLYCERIN; WATER

Dermatouch Hydrating Clear Moisutrizer SPF 25

Active Ingredients

Avobenzone 3.0%

Homosalate 15.0%

Octisalate 5.0%

Purpose

Sunscreen

Warnings

. For external use only. . Do not use on damaged or broken skin.

. When using this product keep out of eyes. Rinse with water to remove.

. Stop use and ask a doctor if rash or irritation occurs or lasts.

. If swallowed, seek medical help or contact a poison control center right away.

. Keep out of reach of children.

. Jar is glass and may shatter if dropped.

Directions

Directions: Apply generously and evenly thirty minutes before sun exposure. Reapply at least every two hours. Use a water-resistant sunscreen if swimming or sweating. Children under six months of age: Consult a doctor.

Inactive Ingredients

Inactive Ingredients: Aqua, SD Alcohol 40-B, Glycerin, Cetearyl Ethylhexanoate, Ammonium Polyacryloyldimethyl Taurate, *CO Glycerin, *CO Humulus Lupulus (Hops) Extract, *CO Lavandula Angustifolia (Lavender) Flower/Leaf/Stem Extract, *CO Calendula Officinalis Flower Extract, *CO Chamomilla Recutita (Matricaria) Flower Extract, *CO Citrus Limon (Lemon) Peel Extract, *CO Cucumis Sativus (Cucumber) Seed Extract, *CO Camellia Sinensis Leaf Extract, *CO Pyrus Malus (Apple) Fruit Extract, *CO Spirulina Platensis Extract, Phenoxyethanol, Ethylhexylglycerin *Certified Organic

INDICATIONS AND USAGE

Uses: . Helps prevent sunburn. . Higher SPF gives more sunburn protection. . If used as directed with other sun protection measures (see Directions), decreases the risk of skin cancer and early skin aging caused by the sun.

KEEP OUT OF REACH OF CHILDREN